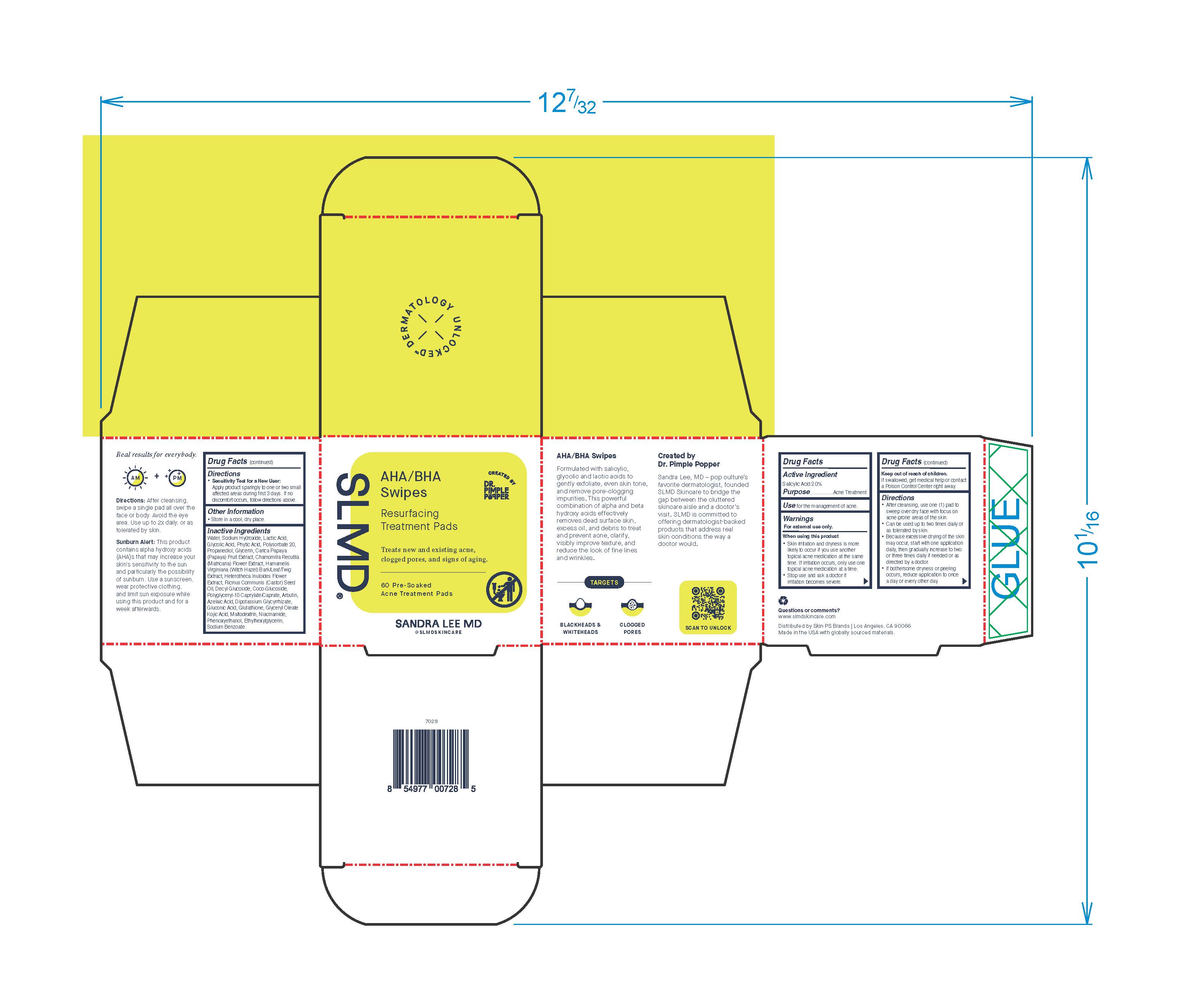 DRUG LABEL: AHA/BHA Swipes
NDC: 73318-7004 | Form: SWAB
Manufacturer: SKIN PS Brands
Category: otc | Type: HUMAN OTC DRUG LABEL
Date: 20251230

ACTIVE INGREDIENTS: SALICYLIC ACID 2 g/100 mL
INACTIVE INGREDIENTS: POLYGLYCERYL-10 CAPRYLATE; PHENOXYETHANOL; ETHYLHEXYLGLYCERIN; AZELAIC ACID; WATER; FYTIC ACID; GLYCYRRHIZINATE DIPOTASSIUM; DECYL GLUCOSIDE; COCO GLUCOSIDE; GLYCERYL OLEATE; GLUCONIC ACID; SODIUM BENZOATE; HETEROTHECA INULOIDES FLOWER; RICINUS COMMUNIS SEED; SODIUM HYDROXIDE; GLYCOLIC ACID; LACTIC ACID, L-; POLYSORBATE 20; CARICA PAPAYA WHOLE; KOJIC ACID; NIACINAMIDE; PROPANEDIOL; GLYCERIN; MATRICARIA CHAMOMILLA FLOWERING TOP; HAMAMELIS VIRGINIANA WHOLE; MALTODEXTRIN; ARBUTIN; GLUTATHIONE

AHA/BHA Swipes

Active Ingredient

Salicylic Acid 2.0%

Purpose

Acne Treatment

Use

For the management of acne

Warnings

For external use only

When using this product

Skin irritation and dryness is more likely to occur if you use another topical acne medication at the same time.If irritation occurs, only use one topical acne medication at a time.

Keep out of reach of children

If swallowed, get medical help or contact a Poison Control Center right away.

Directions

• after cleansing, use one (1) pad to sweep
over dry face with focus on acne-prone
areas of the skin
• Can be used up to two times daily or as
tolerated by skin
• Because excessive drying of the skin may
occur, start with one application daily, then
gradually increase to two or three times
daily if needed or as directed by a doctor
• If bothersome dryness or peeling occurs,
reduce application to once a day or every
other day.
• Sensitivity Test for a New User:
apply product sparingly to one or two small
affected areas during first 3 days. If no
discomfort occurs, follow directions above.

Other Information

Store in a cool, dry place.

Inactive ingredients

Water, Sodium Hydroxide, Lactic Acid, Glycolic Acid, Phytic Acid, Polysorbate 20, Propanediol, Glycerin, Carica Papaya (Papaya) Fruit Extract, Chamomilla Recutita (Matricaria) Flower Extract, Hamamelis Virginiana (Witch Hazel) Bark/Leaf/Twig Extract, Heterotheca Inuloides Flower Extract, Ricinus Communis (Castor) Seed Oil, Decyl Glucoside, Coco-Glucoside, Polyglyceryl-10 Caprylate/Caprate, Arbutin, Azelaic Acid, Dipotassium Glycyrrhizate, Gluconic Acid, Glutathione, Glyceryl Oleate, Kojic Acid, Maltodextrin, Niacinamide, Phenoxyethanol, Ethylhexylglycerin, Sodium Benzoate.

Questions or comments?

slmdskincare.com

Label

SLMD Created By Dr. Pimple Popper

AHA/BHA Swipes

Resurfacing Treatment Pads

Treats new and existing acne, clogged pores, and signs of aging.

60 Pre-Soaked

Acne Treatment Pads

SANDRA LEE MD

@slmdskincare

AHA/BHA Swipes

Formulated with salicylic, glycolic and lactic acids to gently exfoliate, even skin tone, and remove pore-clogging impurities. This powerful combination of alpha and beta hydroxy acids effectively removes dead surface skin, excess oil, and debris to treat and prevent acne, clarify, visibly improve texture, and reduce the look of fine lines and wrinkles.

TARGETS

BLACKHEADS & WHITEHEADS

CLOGGED PORES

Created by Dr. Pimple Popper

Sandra Lee, MD - pop culture's favorite dermatologist, founded SLMD Skincare to bridge the gap between the cluttered skincare aisle and a doctor's visit. SLMD is committed to offering dermatologist-backed products that address real skin conditions the way a doctor would.

Real results for everybody

Directions:After cleansing, swipe a single pad all over the face or body. Avoid the eye area. Use up to 2x daily, or as tolerated by skin.

Sunburn Alert:This product contains alpha hydroxy acids (AHA)s that may increase your skin's sensitivity to the sun and particularly the possibility of sunburn. Use a sunscreen, wear protective clothing, and limit sun exposure while using this product and for a week afterward

www.slmdskincare.com

Distributed by Skin PS Brands | Los Angeles, CA 90066

Made in the USA with globally sourced materials.